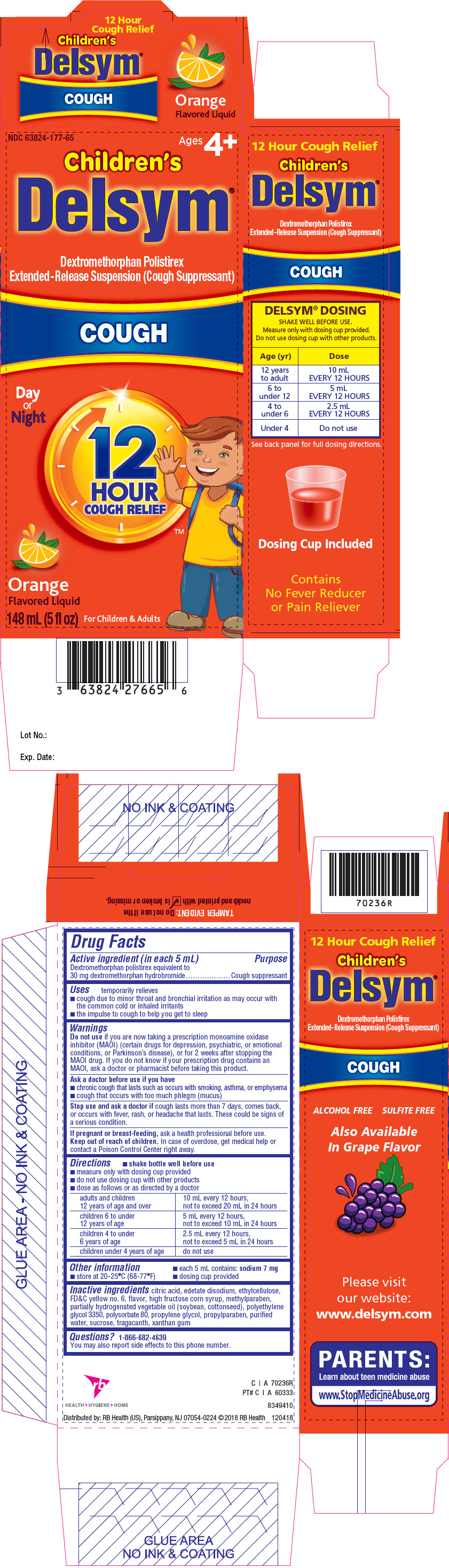 DRUG LABEL: Delsym (Dextromethorphan)
NDC: 63824-177 | Form: SUSPENSION, EXTENDED RELEASE
Manufacturer: RB Health (US) LLC
Category: otc | Type: HUMAN OTC DRUG LABEL
Date: 20240408

ACTIVE INGREDIENTS: DEXTROMETHORPHAN 30 mg/5 mL
INACTIVE INGREDIENTS: POLISTIREX; CITRIC ACID MONOHYDRATE; EDETATE DISODIUM; ETHYLCELLULOSE, UNSPECIFIED; FD&C YELLOW NO. 6; HIGH FRUCTOSE CORN SYRUP; METHYLPARABEN; POLYETHYLENE GLYCOL 3350; POLYSORBATE 80; PROPYLENE GLYCOL; PROPYLPARABEN; WATER; SUCROSE; TRAGACANTH; XANTHAN GUM

Delsym®(Dextromethorphan) Suspension
Extended-Release

Drug Facts

Active ingredient (in each 5 mL)

Dextromethorphan polistirex equivalent to 30 mg dextromethorphan hydrobromide

Purpose

Cough suppressant

Uses

temporarily relieves

- cough due to minor throat and bronchial irritation as may occur with the common cold or inhaled irritants
- the impulse to cough to help you get to sleep

Warnings

DO NOT USE

Do not useif you are now taking a prescription monoamine oxidase inhibitor (MAOI) (certain drugs for depression, psychiatric, or emotional conditions, or Parkinson's disease), or for 2 weeks after stopping the MAOI drug. If you do not know if your prescription drug contains an MAOI, ask a doctor or pharmacist before taking this product.

Ask a doctor before use if you have

- chronic cough that lasts such as occurs with smoking, asthma, or emphysema
- cough that occurs with too much phlegm (mucus)

Stop use and ask a doctor ifcough lasts more than 7 days, comes back, or occurs with fever, rash, or headache that lasts. These could be signs of a serious condition.

PREGNANCY OR BREAST FEEDING

If pregnant or breast-feeding,ask a health professional before use.

Keep out of reach of children.In case of overdose, get medical help or contact a Poison Control Center right away.

Directions

- shake bottle well before use
- measure only with dosing cup provided
- do not use dosing cup with other products
- dose as follows or as directed by a doctor

adults and children 12 years of age and over | 10 mL every 12 hours, not to exceed 20 mL in 24 hours
children 6 to under 12 years of age | 5 mL every 12 hours, not to exceed 10 mL in 24 hours
children 4 to under 6 years of age | 2.5 mL every 12 hours, not to exceed 5 mL in 24 hours
children under 4 years of age | do not use

Other information

- each 5 mL contains: sodium 7 mg
- store at 20-25°C (68-77°F)
- dosing cup provided

Inactive ingredients

citric acid, edetate disodium, ethylcellulose, FD&C yellow no. 6, flavor, high fructose corn syrup, methylparaben, partially hydrogenated vegetable oil (soybean, cottonseed), polyethylene glycol 3350, polysorbate 80, propylene glycol, propylparaben, purified water, sucrose, tragacanth, xanthan gum

Questions?

1-866-682-4639

You may also report side effects to this phone number.

Distributed by: RB Health (US), Parsippany, NJ 07054-0224

PRINCIPAL DISPLAY PANEL - 148 mL Bottle Carton

NDC 63824-177-65
Ages 4+

Children's
Delsym®

Dextromethorphan Polistirex
Extended-Release Suspension (Cough Suppressant)

COUGH

Day
or
Night

12
HOUR
COUGH RELIEF ™

Orange
Flavored Liquid

148 mL (5 fl oz)
For Children & Adults